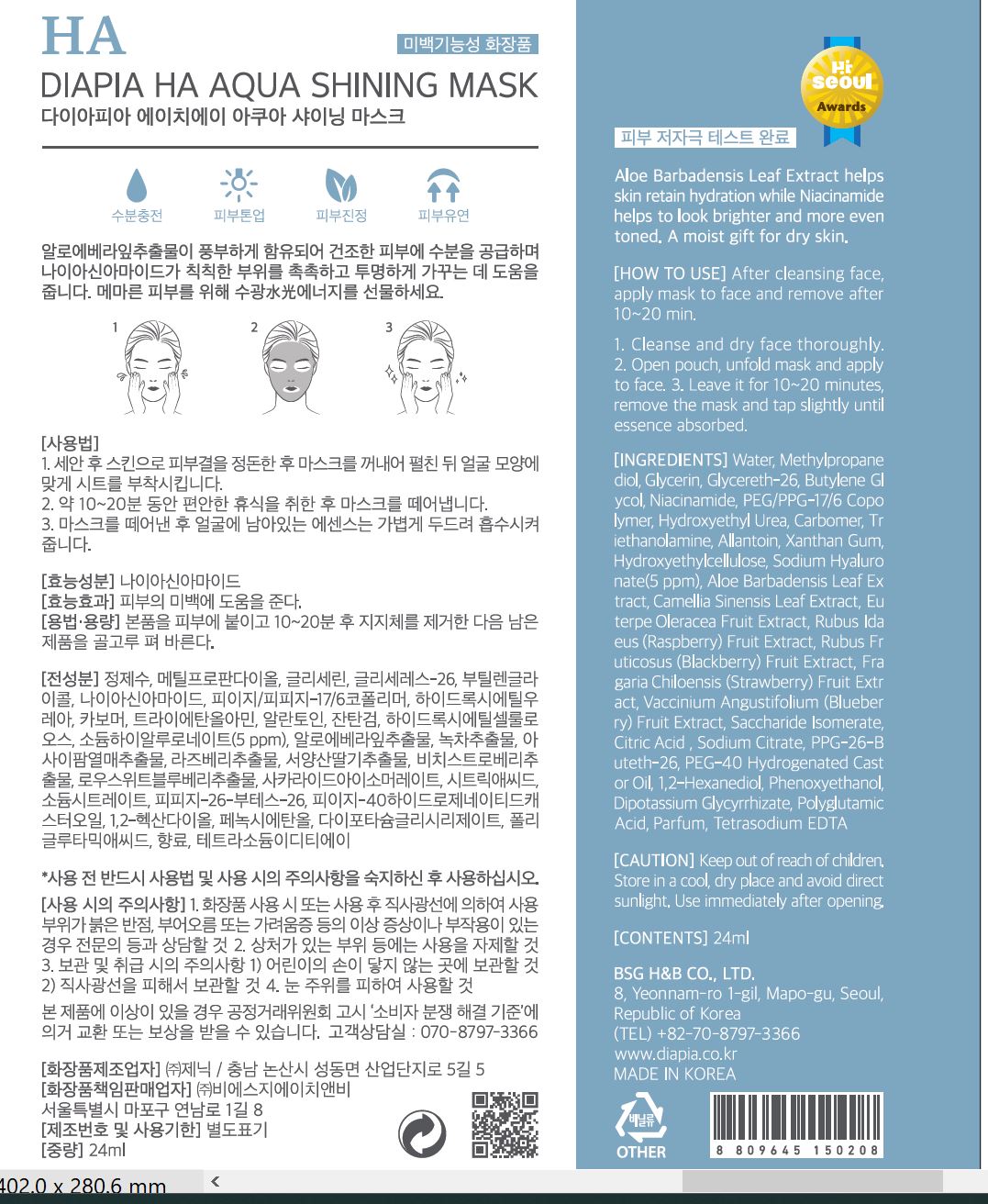 DRUG LABEL: DIAPIA HA Aqua Shining Mask
NDC: 71857-0019 | Form: LIQUID
Manufacturer: BSG H & B Co., Ltd.
Category: otc | Type: HUMAN OTC DRUG LABEL
Date: 20211210

ACTIVE INGREDIENTS: NIACINAMIDE 2 g/100 mL
INACTIVE INGREDIENTS: WATER

Drug Facts

ACTIVE INGREDIENT

Niacinamide

INACTIVE INGREDIENT

Water
Methylpropanediol
Glycerin
Water
Glycereth-26
Butylene Glycol
PEG/PPG-17/6 Copolymer
Water
Hydroxyethyl Urea
1,2-Hexanediol
Phenoxyethanol
Triethanolamine
Water
Water
Butylene Glycol
Sodium Hyaluronate
Phenoxyethanol
Saccharide Isomerate
Water
Sodium Citrate
Citric Acid
PPG-26-Buteth-26
PEG-40 Hydrogenated Castor Oil
Water
Dipotassium Glycyrrhizate
Carbomer
Allantoin
Hydroxyethylcellulose
Sodium Nitrate
Xanthan Gum
Water
Butylene Glycol
Vaccinium Angustifolium (Blueberry) Fruit Extract
Rubus Idaeus (Raspberry) Fruit Extract
Rubus Fruticosus (Blackberry) Fruit Extract
Euterpe Oleracea Fruit Extract
Fragaria Chiloensis (Strawberry) Fruit Extract
Phenoxyethanol
Water
Aloe Barbadensis Leaf Extract
Butylene Glycol
Phenoxyethanol
Water
Camellia Sinensis Leaf Extract
Butylene Glycol
Phenoxyethanol
Tetrasodium EDTA
Parfum
Polyglutamic Acid
Water

PURPOSE

Brightening, anti wrinkle care

keep out of reach of the children

INDICATIONS AND USAGE

after cleansing trim the skin with toner, take out the mask sheet, unfuld and then remove the films

put the upper and lower mask sheets tightly on face according to the shape

after taking a comfortable rest for 10-20 minutes, remove the mask and lightly pat the remaining cream for better absorption

WARNINGS

1.Keep out of reach of children.

2.Store in a cool, dry place and avoid direct sunlight.

3.If abnormal symptoms occur after use, stop use and consult with a skin specialist.

DOSAGE AND ADMINISTRATION

for external use only